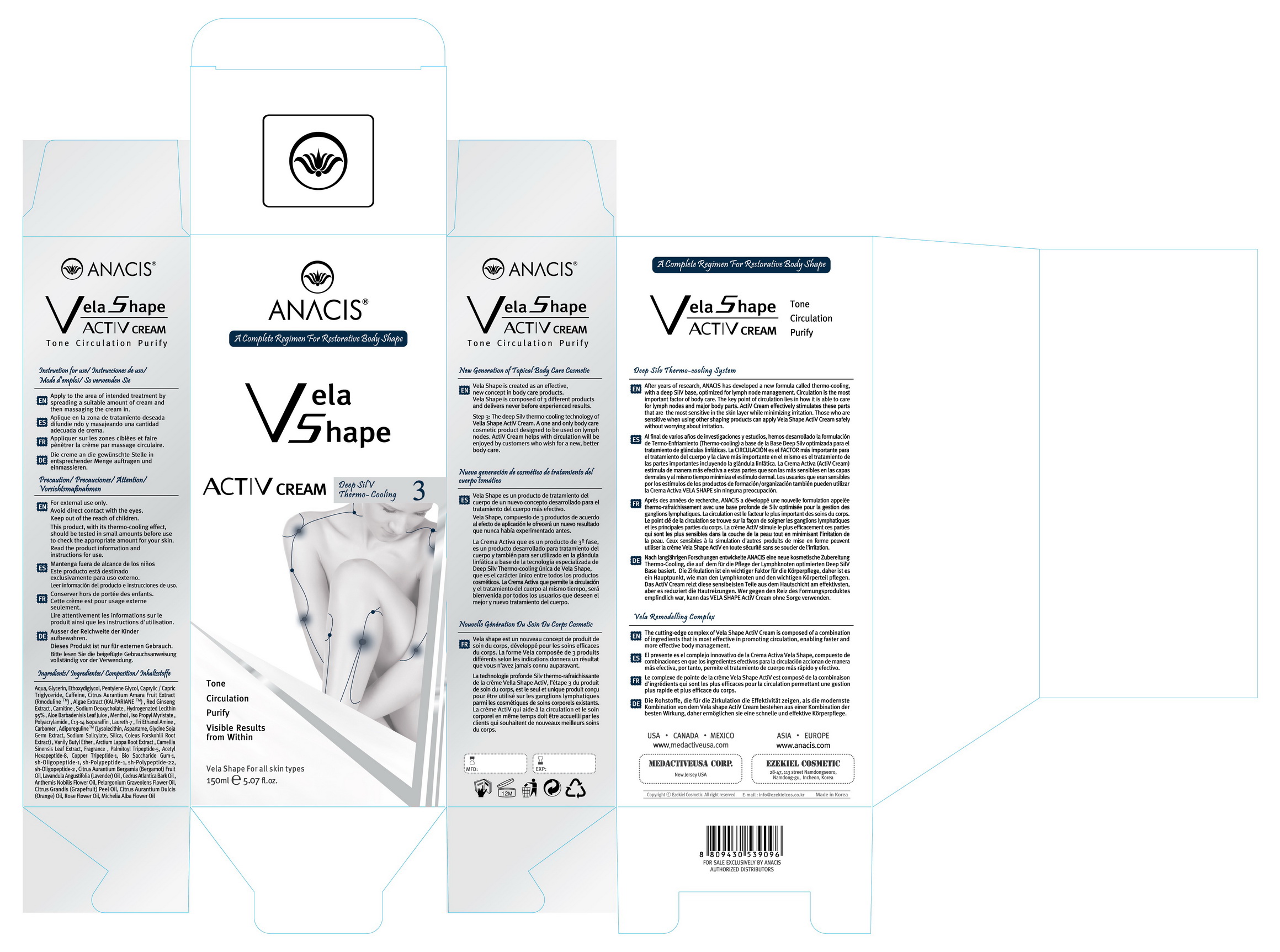 DRUG LABEL: Vela Shape ACTIV  Body firming toning tightening
NDC: 71588-0009 | Form: CREAM
Manufacturer: EZEKIELCOSMETIC CO., LTD
Category: otc | Type: HUMAN OTC DRUG LABEL
Date: 20170818

ACTIVE INGREDIENTS: GLYCERIN 8 g/100 mL
INACTIVE INGREDIENTS: WATER; CAFFEINE; MENTHOL

Drug Facts

ACTIVE INGREDIENT

glycerin

INACTIVE INGREDIENT

water, menthol, caffeine etc

PURPOSE

a complete regimen for restorative body shape

keep out of reach of the children

INDICATIONS AND USAGE

Apply suitable amount of the formula to each area of the body which can include arms, thighs, stomach and/or buttocks and vigorously massage VELA SHAPE RESCULPTING GEL over the targeted areas in a circular motion until full absorption occurs.

WARNINGS

1. If the following symptoms occur after product use, stop using the product immediately and consult a dermatologist (continuous use can exacerbate the symptoms).
1) Occurrence of red spots, swelling, itchiness, and other skin irritation
2) If the symptoms above occur after the application area is exposed to direct sunlight
2. Do not use on open wounds, eczema, and other skin irritations
3. Precaution for Storage and Handling
1) Close the lid after use
2) Keep out of reach of infants and children
3) Do not to store in a place with high/low temperature and exposed to direct sunlight

4. Use as avoiding eye areas.

DOSAGE AND ADMINISTRATION

for external use only